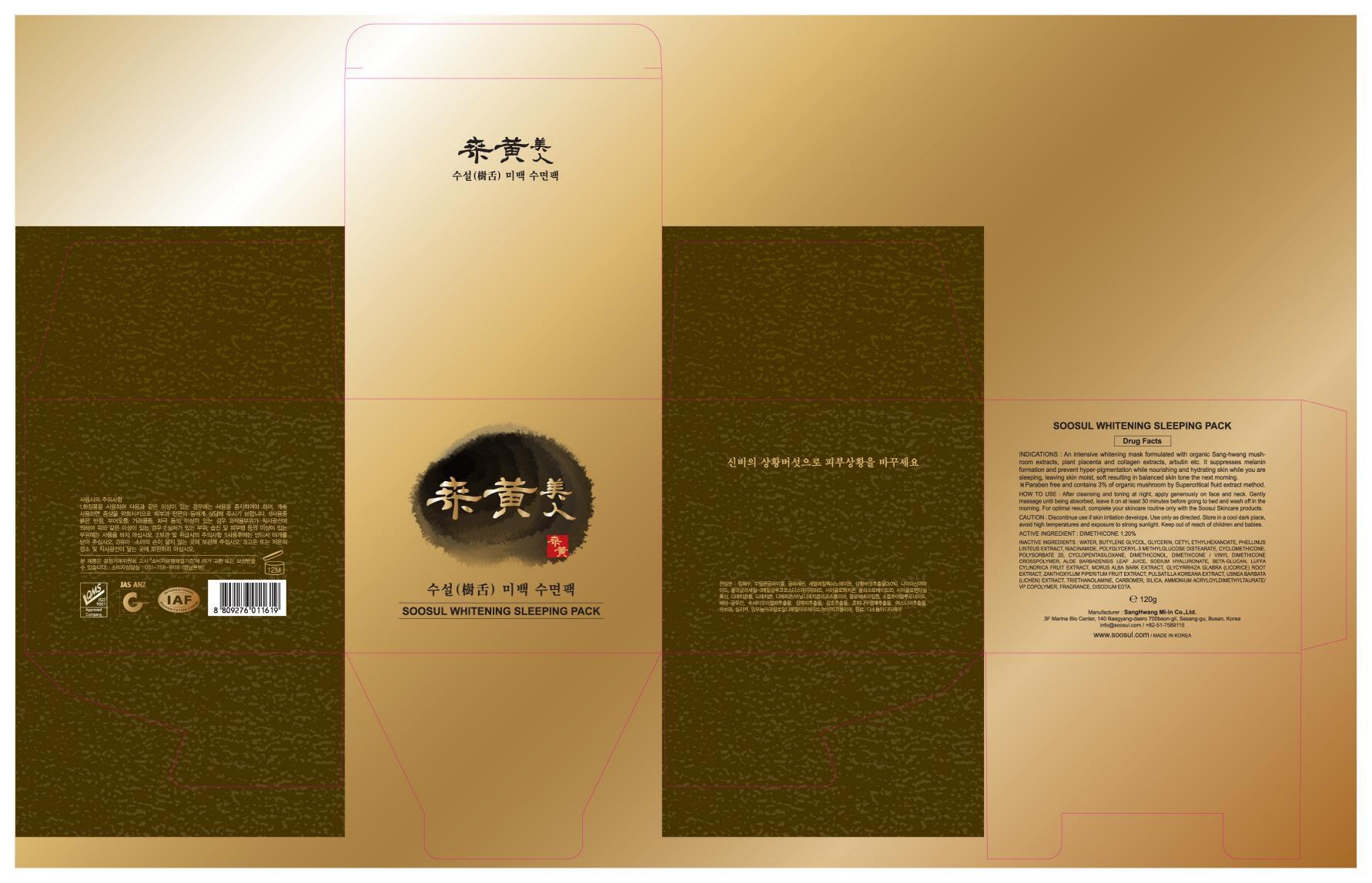 DRUG LABEL: SOOSUL WHITENING SLEEPING PACK
NDC: 69351-030 | Form: CREAM
Manufacturer: Sang Hwang Mi-in Co., Ltd.
Category: otc | Type: HUMAN OTC DRUG LABEL
Date: 20141127

ACTIVE INGREDIENTS: DIMETHICONE 1.44 g/120 g
INACTIVE INGREDIENTS: WATER; GLYCERIN

ACTIVE INGREDIENT

Active Ingredient: DIMETHICONE 1.20%

INACTIVE INGREDIENT

Inactive Ingredients:
WATER, BUTYLENE GLYCOL, GLYCERIN, CETYL ETHYLHEXANOATE, PHELLINUS LINTEUS EXTRACT, NIACINAMIDE, POLYGLYCERYL-3 METHYLGLUCOSE DISTEARATE, CYCLOMETHICONE, POLYSORBATE 20, CYCLOPENTASILOXANE, DIMETHICONOL, DIMETHICONE / VINYL DIMETHICONE CROSSPOLYMER, ALOE BARBADENSIS LEAF JUICE, SODIUM HYALURONATE, BETA-GLUCAN, LUFFA CYLINDRICA FRUIT EXTRACT, MORUS ALBA BARK EXTRACT, GLYCYRRHIZA GLABRA (LICORICE) ROOT EXTRACT, ZANTHOXYLUM PIPERITUM FRUIT EXTRACT, PULSATILLA KOREANA EXTRACT, USNEA BARBATA (LICHEN) EXTRACT, TRIETHANOLAMINE, CARBOMER, SILICA, AMMONIUM ACRYLOYLDIMETHYLTAURATE/ VP COPOLYMER, FRAGRANCE, DISODIUM EDTA

PURPOSE

PURPOSE: SKIN PROTECTANT

Caution

Caution: Discontinue use if skin irritation develops. Use only as directed. Store in a cool dark place, avoid high temperatures and exposure to strong sunlight. Keep out of reach of children and babies.

Keep out of reach of children and babies.

Indications

An intensive whitening mask formulated with organic Sang-hwang mushroom extracts, plant placenta and collagen extracts, arbutin etc. It suppresses melanin formation and prevent hyper-pigmentation while nourishing and hydrating skin while you are sleeping, leaving skin moist, soft resulting in balanced skin tone the next morning.
- Paraben free and contains 3% of organic mushroom by Supercritical fluid extract method.

How to use: After cleansing and toning at night, apply generously on face and neck. Gently massage until being absorbed, leave it on at least 30 minutes before going to bed and wash off in the morning. For optimal result, complete your skincare routine only with the Soosul Skincare products.